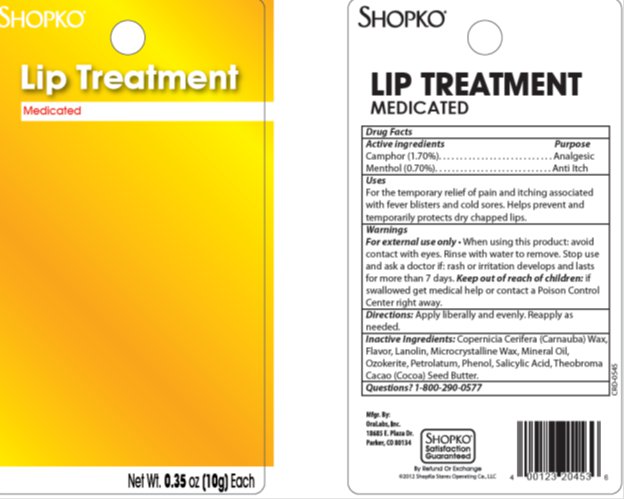 DRUG LABEL: Shopko Medicated Lip Treatment
NDC: 37012-735 | Form: GEL
Manufacturer: Shopko
Category: otc | Type: HUMAN OTC DRUG LABEL
Date: 20130801

ACTIVE INGREDIENTS: CAMPHOR (SYNTHETIC) 1.700 mg/1 g; MENTHOL 0.700 mg/1 g
INACTIVE INGREDIENTS: LIGHT MINERAL OIL 1.053 mg/1 g; PHENOL 0.400 mg/1 g; EUCALYPTUS OIL 0.500 mg/1 g; PETROLATUM 83.947 mg/1 g; CERESIN 1.000 mg/1 g; LANOLIN 8.000 mg/1 g

Drug Facts

Active ingredient

Camphor (1.70%), Menthol (0.70%)

Purpose

Analgesic, Anti-itch

Keep Out of Reach of Children

If swallowed get medical help or contact a Poison Control Center right away.

Uses

For the temporary relief of pain and itching associated with fever blisters and cold sores. Helps prevent and temporarily protects dry chapped lips.

Warnings

For external use only. When using this product: avoid contact with eyes. Rinse with water to remove. Stop use and ask a doctor if: rash or irritation develops and lasts for more than 7 days. Keep out of reach of children: if swallowed get medical help or contact a Poison Control Center right away.

Directions

Apply liberally and evenly. Reapply as needed.

Inactive Ingredients

Copernicia Cerifera (Carnauba) Wax, Flavor, Lanolin, Microcrystalline Wax, Mineral Oil, Ozokerite, Petrolatum, Phenol, Salicylic Acid, Theobroma Cacao (Cocoa) Seed Butter.